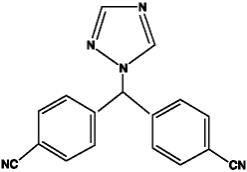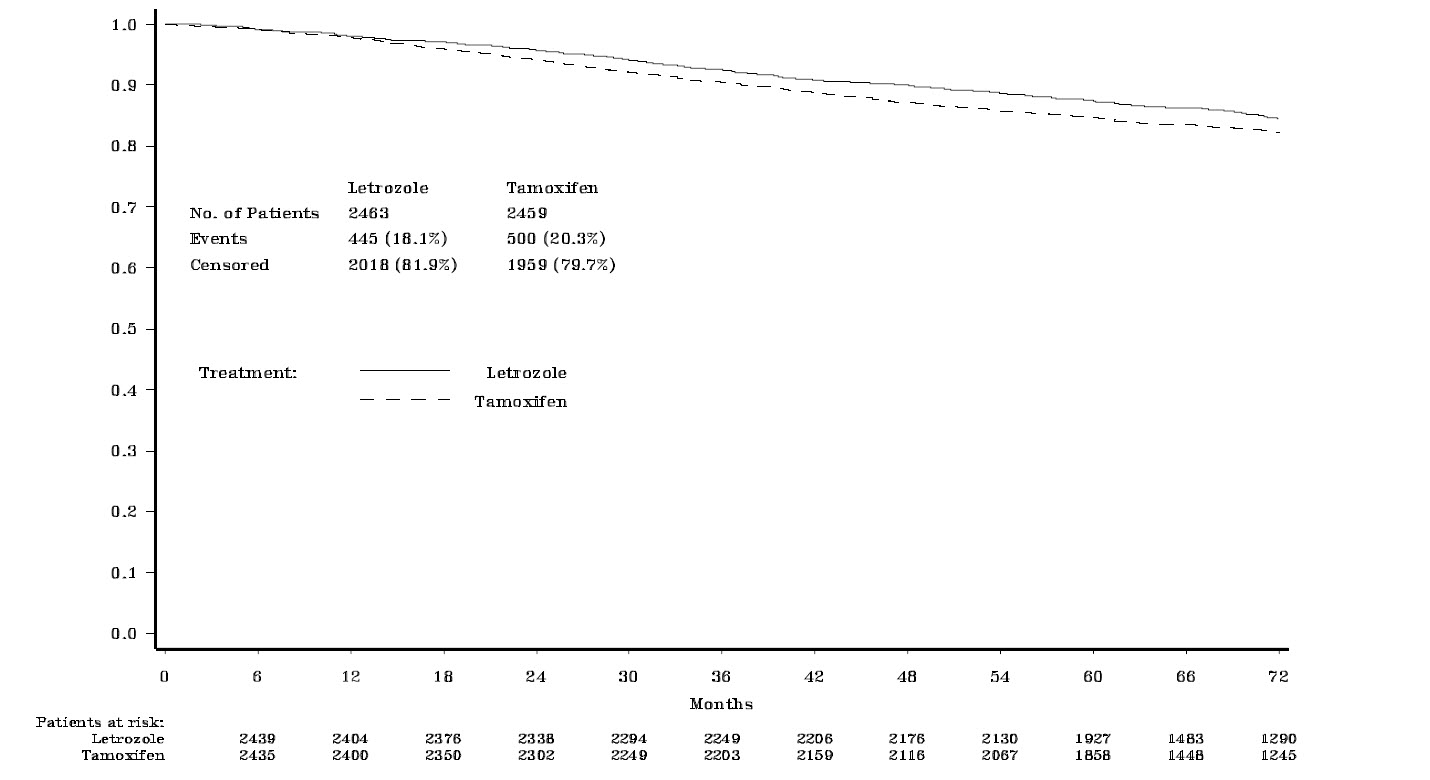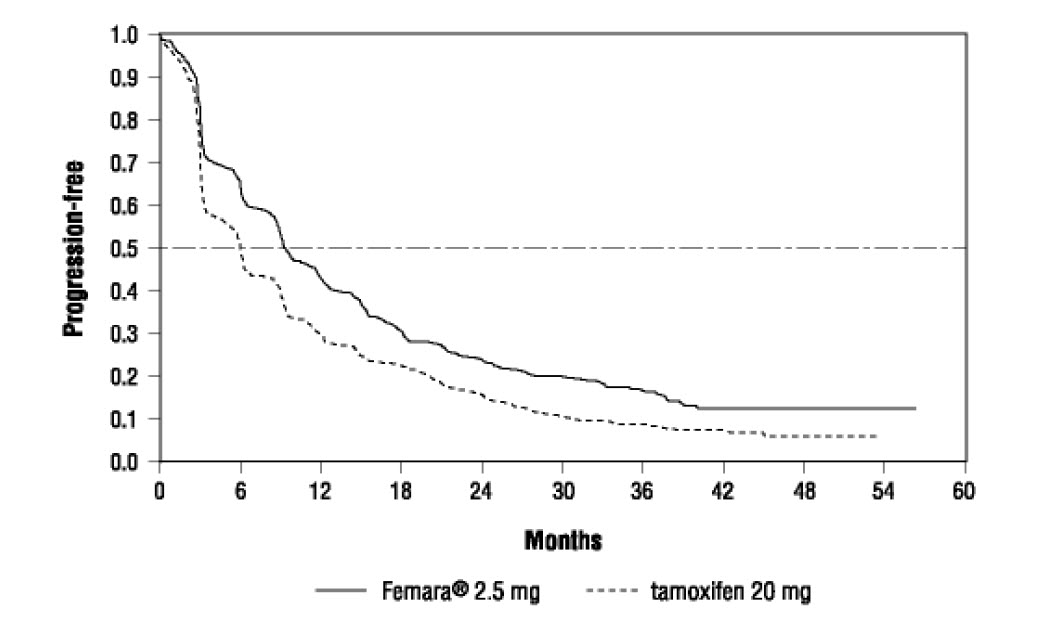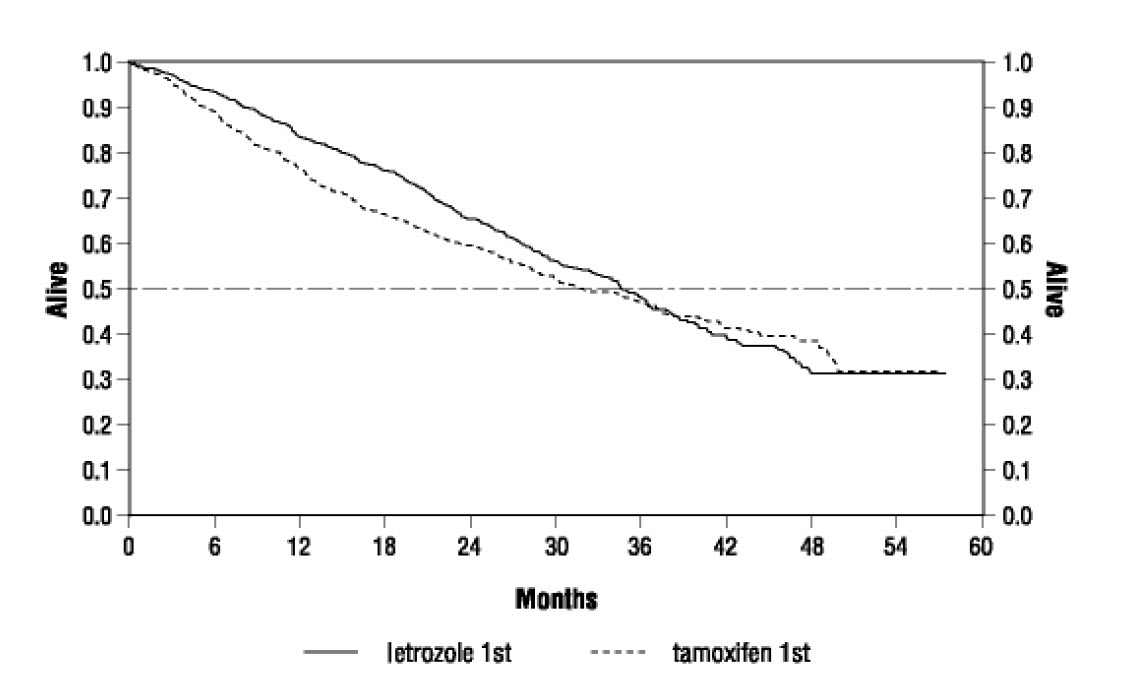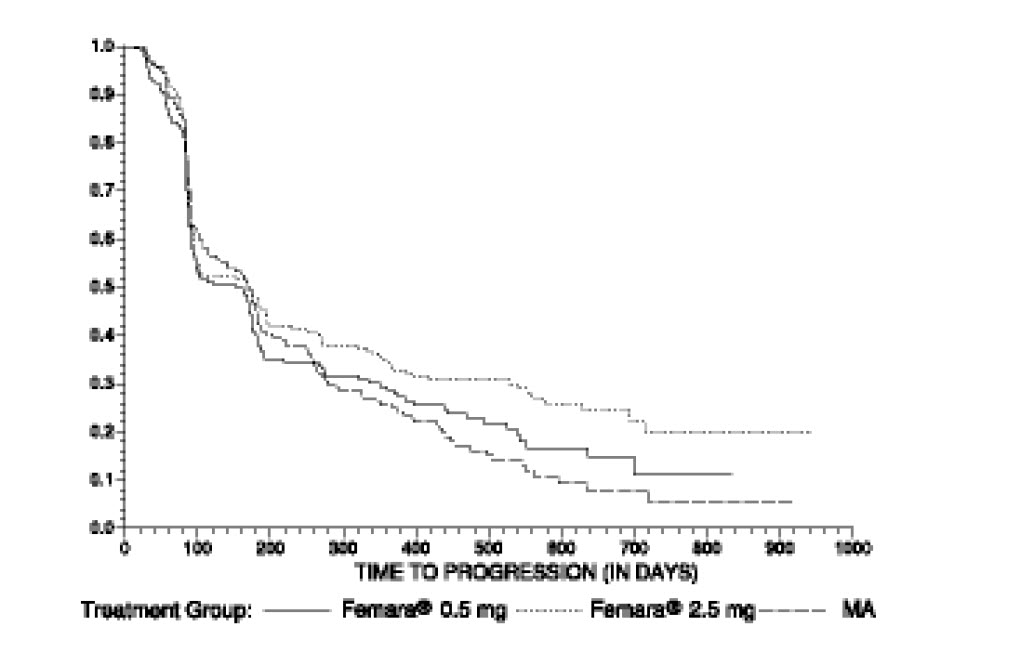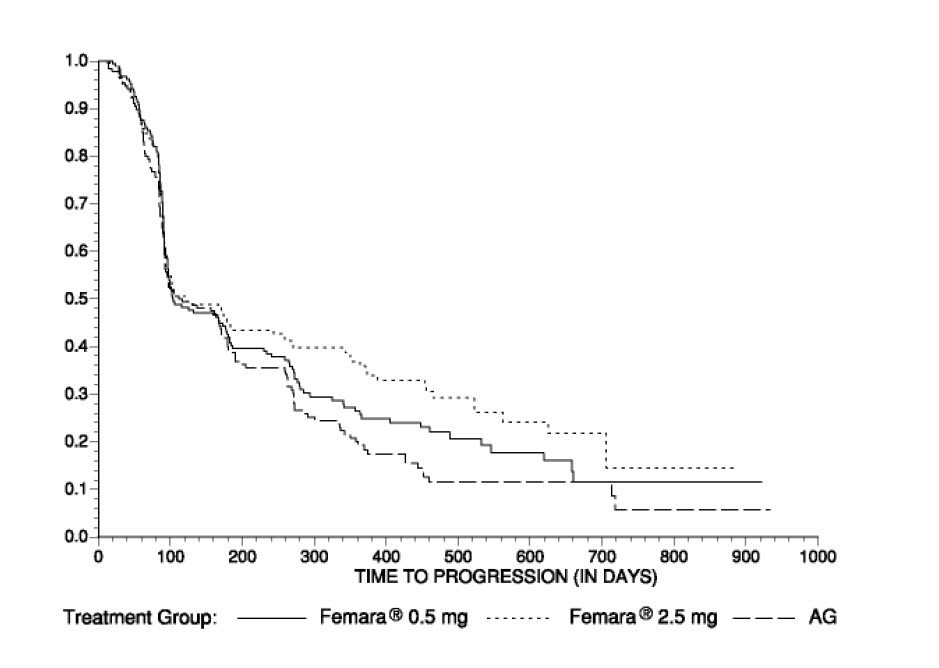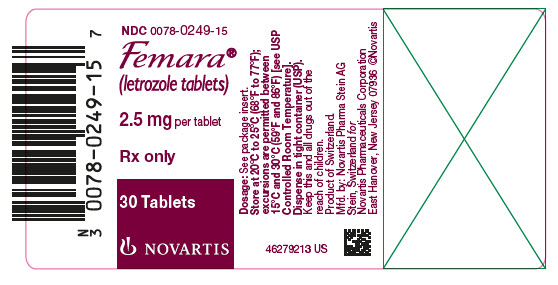 DRUG LABEL: Femara
NDC: 0078-0249 | Form: TABLET, FILM COATED
Manufacturer: Novartis Pharmaceuticals Corporation
Category: prescription | Type: HUMAN PRESCRIPTION DRUG LABEL
Date: 20250821

ACTIVE INGREDIENTS: LETROZOLE 2.5 mg/1 1
INACTIVE INGREDIENTS: SILICON DIOXIDE; FERRIC OXIDE YELLOW; HYPROMELLOSES; LACTOSE MONOHYDRATE; MAGNESIUM STEARATE; STARCH, CORN; CELLULOSE, MICROCRYSTALLINE; POLYETHYLENE GLYCOL; SODIUM STARCH GLYCOLATE TYPE A POTATO; TALC; TITANIUM DIOXIDE

HIGHLIGHTS OF PRESCRIBING INFORMATION

These highlights do not include all the information needed to use FEMARA safely and effectively. See full prescribing information for FEMARA.
FEMARA (letrozole) tablets, for oral use
Initial U.S. Approval: 1997

1 INDICATIONS AND USAGE

Femara is an aromatase inhibitor indicated for:

- Adjuvant treatment of postmenopausal women with hormone receptor positive early breast cancer. (1.1)
- Extended adjuvant treatment of postmenopausal women with early breast cancer who have received prior standard adjuvant tamoxifen therapy. (1.2)
- First and second-line treatment of postmenopausal women with hormone receptor positive or unknown advanced breast cancer. (1.3)

2 DOSAGE AND ADMINISTRATION

Femara tablets are taken orally without regard to meals (2):

- Recommended dose: 2.5 mg once daily. (2.1)
- Patients with cirrhosis or severe hepatic impairment: 2.5 mg every other day. (2.5, 5.3)

3 DOSAGE FORMS AND STRENGTHS

2.5 mg tablets. (3)

4 CONTRAINDICATIONS

- Pregnancy. (4)
- Known hypersensitivity to the active substance, or to any of the excipients. (4)

5 WARNINGS AND PRECAUTIONS

- Decreases in bone mineral density may occur. Consider bone mineral density monitoring. (5.1)
- Increases in total cholesterol may occur. Consider cholesterol monitoring. (5.2)
- Fatigue, dizziness, and somnolence may occur. Exercise caution when operating machinery. (5.4)
- Embryo-Fetal Toxicity: Can cause fetal harm when administered to pregnant women. Obtain a pregnancy test in females of reproductive potential. Advise females of reproductive potential to use effective contraception. (5.6, 8.1, 8.3)

6 ADVERSE REACTIONS

The most common adverse reactions (greater than 20%) were hot flashes, arthralgia; flushing, asthenia, edema, arthralgia, headache, dizziness, hypercholesterolemia, sweating increased, bone pain; and musculoskeletal. (6)

To report SUSPECTED ADVERSE REACTIONS, contact Novartis Pharmaceuticals Corporation at 1-888-669-6682 or FDA at 1-800-FDA-1088 or www.fda.gov/medwatch.

8 USE IN SPECIFIC POPULATIONS

- Lactation: Advise not to breastfeed. (8.2)

FULL PRESCRIBING INFORMATION

1 INDICATIONS AND USAGE

1.1 Adjuvant Treatment of Early Breast Cancer

Femara (letrozole) is indicated for the adjuvant treatment of postmenopausal women with hormone receptor positive early breast cancer.

1.2 Extended Adjuvant Treatment of Early Breast Cancer

Femara is indicated for the extended adjuvant treatment of early breast cancer in postmenopausal women, who have received 5 years of adjuvant tamoxifen therapy. The effectiveness of Femara in extended adjuvant treatment of early breast cancer is based on an analysis of disease-free survival (DFS) in patients treated with Femara for a median of 60 months [see Clinical Studies (14.2, 14.3)].

1.3 First and Second-Line Treatment of Advanced Breast Cancer

Femara is indicated for first-line treatment of postmenopausal women with hormone receptor positive or unknown, locally advanced or metastatic breast cancer. Femara is also indicated for the treatment of advanced breast cancer in postmenopausal women with disease progression following antiestrogen therapy [see Clinical Studies (14.4, 14.5)].

2 DOSAGE AND ADMINISTRATION

2.1 Recommended Dose

The recommended dose of Femara is one 2.5 mg tablet administered once a day, without regard to meals.

2.2 Use in Adjuvant Treatment of Early Breast Cancer

In the adjuvant setting, the optimal duration of treatment with letrozole is unknown. In both the adjuvant study and the post approval adjuvant study, median treatment duration was 5 years. Treatment should be discontinued at relapse [see Clinical Studies (14.1)].

2.3 Use in Extended Adjuvant Treatment of Early Breast Cancer

In the extended adjuvant setting, the optimal treatment duration with Femara is not known. The planned duration of treatment in the study was 5 years. In the final updated analysis, conducted at a median follow-up of 62 months, the median treatment duration for Femara was 60 months. Seventy-one percent (71%) of patients were treated for at least 3 years and 58% of patients completed at least 4.5 years of extended adjuvant treatment. The treatment should be discontinued at tumor relapse [see Clinical Studies (14.2)].

2.4 Use in First and Second-Line Treatment of Advanced Breast Cancer

In patients with advanced disease, treatment with Femara should continue until tumor progression is evident [see Clinical Studies (14.4, 14.5)].

2.5 Use in Hepatic Impairment

No dosage adjustment is recommended for patients with mild to moderate hepatic impairment, although Femara blood concentrations were modestly increased in subjects with moderate hepatic impairment due to cirrhosis. The dose of Femara in patients with cirrhosis and severe hepatic dysfunction should be reduced by 50% [see Warnings and Precautions (5.3)]. The recommended dose of Femara for such patients is 2.5 mg administered every other day. The effect of hepatic impairment on Femara exposure in noncirrhotic cancer patients with elevated bilirubin levels has not been determined.

2.6 Use in Renal Impairment

No dosage adjustment is required for patients with renal impairment if creatinine clearance is greater than or equal to 10 mL/min [see Clinical Pharmacology (12.3)].

3 DOSAGE FORMS AND STRENGTHS

2.5 mg tablets: dark yellow, film-coated, round, slightly biconvex, with beveled edges (imprinted with the letters ‘FV’ on one side and ‘CG’ on the other side).

4 CONTRAINDICATIONS

- Pregnancy: Letrozole can cause fetal harm [see Use in Specific Populations (8.1)].
- Known hypersensitivity to the active substance, or to any of the excipients [see Adverse Reactions (6)].

5 WARNINGS AND PRECAUTIONS

5.1 Bone Effects

Use of Femara may cause decreases in bone mineral density (BMD). Consideration should be given to monitoring BMD. Results of a safety study to evaluate safety in the adjuvant setting comparing the effect on lumbar spine (L2-L4) BMD of adjuvant treatment with letrozole to that with tamoxifen showed at 24 months a median decrease in lumbar spine BMD of 4.1% in the letrozole arm compared to a median increase of 0.3% in the tamoxifen arm (difference = 4.4%) (P < 0.0001) [see Adverse Reactions (6)]. Updated results from the BMD substudy (MA-17B) in the extended adjuvant setting demonstrated that at 2 years patients receiving letrozole had a median decrease from baseline of 3.8% in hip BMD compared to a median decrease of 2.0% in the placebo group. The changes from baseline in lumbar spine BMD in letrozole and placebo treated groups were not significantly different [see Adverse Reactions (6)].

In the adjuvant trial (BIG 1-98) the incidence of bone fractures at any time after randomization was 14.7% for letrozole and 11.4% for tamoxifen at a median follow-up of 96 months. The incidence of osteoporosis was 5.1% for letrozole and 2.7% for tamoxifen [see Adverse Reactions (6)]. In the extended adjuvant trial (MA-17), the incidence of bone fractures at any time after randomization was 13.3% for letrozole and 7.8% for placebo at a median follow-up of 62 months. The incidence of new osteoporosis was 14.5% for letrozole and 7.8% for placebo [see Adverse Reactions (6)].

5.2 Cholesterol

Consideration should be given to monitoring serum cholesterol. In the adjuvant trial (BIG 1-98), hypercholesterolemia was reported in 52.3% of letrozole patients and 28.6% of tamoxifen patients. Grade 3-4 hypercholesterolemia was reported in 0.4% of letrozole patients and 0.1% of tamoxifen patients. Also in the adjuvant setting, an increase of greater than or equal to 1.5 x upper limit of normal (ULN) in total cholesterol (generally nonfasting) was observed in patients on monotherapy who had baseline total serum cholesterol within the normal range (i.e., less than = 1.5 x ULN) in 155/1843 (8.4%) patients on letrozole vs 71/1840 (3.9%) patients on tamoxifen Lipid lowering medications were required for 29% of patients on letrozole and 20% on tamoxifen [see Adverse Reactions (6)].

5.3 Hepatic Impairment

Subjects with cirrhosis and severe hepatic impairment who were dosed with 2.5 mg of Femara experienced approximately twice the exposure to Femara as healthy volunteers with normal liver function [see Clinical Pharmacology (12.3)]. Therefore, a dose reduction is recommended for this patient population. The effect of hepatic impairment on Femara exposure in cancer patients with elevated bilirubin levels has not been determined [see Dosage and Administration (2.5)].

5.4 Fatigue and Dizziness

Because fatigue, dizziness, and somnolence have been reported with the use of Femara, caution is advised when driving or using machinery until it is known how the patient reacts to Femara use.

5.5 Laboratory Test Abnormalities

No dose-related effect of Femara on any hematologic or clinical chemistry parameter was evident. Moderate decreases in lymphocyte counts, of uncertain clinical significance, were observed in some patients receiving Femara 2.5 mg. This depression was transient in about half of those affected. Two patients on Femara developed thrombocytopenia; relationship to the study drug was unclear. Patient withdrawal due to laboratory abnormalities, whether related to study treatment or not was infrequent.

5.6 Embryo-Fetal Toxicity

Based on post-marketing reports, findings from animal studies and the mechanism of action, Femara can cause fetal harm and is contraindicated for use in pregnant women. In post-marketing reports, use of letrozole during pregnancy resulted in cases of spontaneous abortions and congenital birth defects. Letrozole caused embryo-fetal toxicities in rats and rabbits at maternal exposures that were below the maximum recommended human dose (MHRD) on a mg/m^2 basis. Advise pregnant women of the potential risk to a fetus. Advise females of reproductive potential to use effective contraception during therapy with Femara and for at least 3 weeks after the last dose [see Adverse Reactions (6.2), Use in Specific Populations (8.1, 8.3), and Clinical Pharmacology (12.1)].

6 ADVERSE REACTIONS

The following adverse reactions are discussed in greater detail in other sections of the labeling.

- Bone effects [see Warnings and Precautions (5.1)]
- Increases in cholesterol [see Warnings and Precautions (5.2)]
- Fatigue and Dizziness [see Warnings and Precautions (5.4)]

6.1 Clinical Trials Experience

Because clinical trials are conducted under widely varying conditions, adverse reactions rates observed in the clinical trials of a drug cannot be directly compared to rates in the clinical trials of another drug and may not reflect the rates observed in practice.

Adjuvant Treatment of Early Breast Cancer

In study, BIG 1-98, the median treatment duration of adjuvant treatment was 60 months and the median duration of follow-up for safety was 96 months for patients receiving Femara and tamoxifen.

Certain adverse reactions were prospectively specified for analysis (see Table 1), based on the known pharmacologic properties and side effect profiles of the two drugs.

Adverse reactions were analyzed irrespective of whether a symptom was present or absent at baseline. Most adverse reactions reported (approximately 75% of patients who reported AEs) were Grade 1 or Grade 2 applying the Common Toxicity Criteria (CTC) Version 2.0/Common Terminology Criteria for Adverse Events (CTCAE), Version 3.0. Table 1 describes adverse reactions (Grades 1-4 and Grades 3-4) irrespective of relationship to study treatment in the adjuvant trial for the monotherapy arms analysis (safety population).

Table 1: Patients With Adverse Reactions (CTC Grades 1-4) in the Adjuvant Study – Monotherapy Arms Analysis (Median Follow-up 96 Months; Median Treatment 60 Months)
 | Grades 1-4 |  |  |  | Grades 3-4
 | Femara |  | Tamoxifen |  | Femara |  | Tamoxifen
Adverse Reactions | N = 2448 |  | N = 2447 |  | N = 2448 |  | N = 2447
 | n (%) |  | n (%) |  | n (%) |  | n (%)
Patients with any adverse reaction | 2309 | (94.3) | 2212 | (90.4) | 636 | (26.0) | 606 | (24.8)
Hypercholesterolemia* | 1280 | (52.3) | 700 | (28.6) | 11 | (0.4) | 6 | (0.2)
Hot flashes* | 819 | (33.5) | 929 | (38.0) | - | - | - | -
Arthralgia/arthritis* | 621 | (25.4) | 504 | (20.6) | 84 | (3.4) | 50 | (2.0)
Bone fractures^1 | 361 | (14.7) | 280 | (11.4) | - | - | - | -
Night sweats* | 356 | (14.5) | 426 | (17.4) | - | - | - | -
Weight increase* | 317 | (12.9) | 378 | (15.4) | 27 | (1.1) | 39 | (1.6)
Nausea* | 284 | (11.6) | 277 | (11.3) | 6 | (0.2) | 9 | (0.4)
Bone fractures**^2 | 249 | (10.2) | 175 | (7.2) | - | - | - | -
Fatigue (lethargy, malaise, asthenia)* | 235 | (9.6) | 250 | (10.2) | 6 | (0.2) | 7 | (0.3)
Myalgia* | 221 | (9.0) | 212 | (8.7) | 18 | (0.7) | 14 | (0.6)
Vaginal bleeding* | 129 | (5.3) | 320 | (13.1) | 1 | (< 0.1) | 8 | (0.3)
Edema* | 164 | (6.7) | 160 | (6.5) | 3 | (0.1) | 1 | (< 0.1)
Weight decrease | 140 | (5.7) | 129 | (5.3) | 8 | (0.3) | 5 | (0.2)
Osteoporosis** | 126 | (5.1) | 67 | (2.7) | 10 | (0.4) | 5 | (0.2)
Back pain | 125 | (5.1) | 136 | (5.6) | 7 | (0.3) | 11 | (0.4)
Bone pain | 123 | (5.0) | 109 | (4.5) | 6 | (0.2) | 4 | (0.2)
Depression | 119 | (4.9) | 114 | (4.7) | 16 | (0.7) | 14 | (0.6)
Vaginal irritation* | 112 | (4.6) | 77 | (3.1) | 2 | (< 0.1) | 2 | (< 0.1)
Headache* | 105 | (4.3) | 94 | (3.8) | 8 | (0.3) | 4 | (0.2)
Pain in extremity | 103 | (4.2) | 79 | (3.2) | 6 | (0.2) | 4 | (0.2)
Osteopenia* | 87 | (3.6) | 76 | (3.1) | 0 | - | 3 | (0.1)
Dizziness/light-headedness* | 84 | (3.4) | 80 | (3.3) | 1 | (< 0.1) | 6 | (0.2)
Alopecia | 83 | (3.4) | 84 | (3.4) | - | - | - | -
Vomiting* | 80 | (3.3) | 80 | (3.3) | 3 | (0.1) | 5 | (0.2)
Cataract* | 49 | (2.0) | 54 | (2.2) | 16 | (0.7) | 17 | (0.7)
Constipation* | 49 | (2.0) | 71 | (2.9) | 3 | (0.1) | 1 | (< 0.1)
Myocardial infarction^1 | 42 | (1.7) | 28 | (1.1) | - | - | - | -
Breast pain* | 37 | (1.5) | 43 | (1.8) | 1 | (< 0.1) | - | -
Anorexia* | 20 | (0.8) | 20 | (0.8) | 1 | (< 0.1) | 1 | (< 0.1)
Endometrial proliferation disorders* | 14 | (0.6) | 86 | (3.5) | 0 | - | 14 | (0.6)
Ovarian cyst* | 11 | (0.4) | 18 | (0.7) | 4 | (0.2) | 4 | (0.2)
Endometrial hyperplasia/cancer**^1 | 11 | (0.4) | 72 | (2.9) | - | - | - | -
Endometrial hyperplasia/cancer**,^3 | 6/1909 | (0.3) | 57/1943 | (2.9) | - | - | - | -
Other endometrial disorders* | 2 | (< 0.1) | 3 | (0.1) | 0 | - | 0 | -
Myocardial infarction**^2 | 24 | (1.0) | 12 | (0.5) | - | - | - | -
Myocardial ischemia | 6 | (0.2) | 9 | (0.4) | - | - | - | -
Cerebrovascular accident/TIA**^1 | 74 | (3.0) | 68 | (2.8) | - | - | - | -
Cerebrovascular accident/TIA**^2 | 51 | (2.1) | 47 | (1.9) | - | - | - | -
Angina requiring surgery**^1 | 35 | (1.4) | 33 | (1.3) | - | - | - | -
Angina requiring surgery**^2 | 25 | (1.0) | 25 | (1.0) | - | - | - | -
Thromboembolic event**^1 | 79 | (3.2) | 113 | (4.6) | - | - | - | -
Thromboembolic event**^2 | 51 | (2.1) | 89 | (3.6) | - | - | - | -
Cardiac failure^1 | 39 | (1.6) | 34 | (1.4) | - | - | - | -
Cardiac failure^2 | 27 | (1.1) | 15 | (0.6) | - | - | - | -
Hypertension^1 | 160 | (6.5) | 175 | (7.2) | - | - | - | -
Hypertension^2 | 138 | (5.6) | 139 | (5.7) | - | - | - | -
Other cardiovascular**^1 | 172 | (7.0) | 174 | (7.1) | - | - | - | -
Other cardiovascular**^2 | 120 | (4.9) | 119 | (4.9) | - | - | - | -
Second primary malignancy^1 | 129 | (5.3) | 150 | (6.1) | - | - | - | -
Second primary malignancy^2 | 54 | (2.2) | 79 | (3.2) | - | - | - | -
*Target events pre-specified for analysis
**Events pre-printed on CRF
^1At median follow-up of 96 months (i.e., any time after randomization) for Femara (range up to 144 months) and 95 months for tamoxifen (range up to 143 months).
^2At median treatment duration of 60 months (i.e. during treatment + 30 days after discontinuation of treatment) for Femara and tamoxifen (range up to 68 months).
^3Excluding women who had undergone hysterectomy before study entry.
TIA = Transient ischemic attack.
Note: Cardiovascular events (including cerebrovascular and thromboembolic events), skeletal and urogenital/endometrial events and second primary malignancies were collected life -long. All of these events were assumed to be of CTC Grade 3 to 5 and were not individually graded.

When considering all grades during study treatment, a higher incidence of events was seen for Femara regarding fractures (10.1% vs 7.1%), myocardial infarctions (1.0% vs 0.5%), and arthralgia (25.2% vs 20.4%) (Femara vs tamoxifen respectively). A higher incidence was seen for tamoxifen regarding thromboembolic events (2.1% vs 3.6%), endometrial hyperplasia/cancer (0.3% vs 2.9%), and endometrial proliferation disorders (0.3% vs 1.8%) (Femara vs tamoxifen respectively).

At a median follow-up of 96 months, a higher incidence of events was seen for Femara (14.7%) than for tamoxifen (11.4%) regarding fractures. A higher incidence was seen for tamoxifen compared to Femara regarding thromboembolic events (4.6% vs 3.2%), and endometrial hyperplasia or cancer (2.9% vs 0.4%) (tamoxifen vs Femara, respectively).

Bone Study: Results of a safety trial in 263 postmenopausal women with resected receptor positive early breast cancer in the adjuvant setting comparing the effect on lumbar spine (L2-L4) BMD of adjuvant treatment with letrozole to that with tamoxifen showed at 24 months a median decrease in lumbar spine BMD of 4.1% in the letrozole arm compared to a median increase of 0.3% in the tamoxifen arm (difference = 4.4%) (P < 0.0001). No patients with a normal BMD at baseline became osteoporotic over the 2 years and only 1 patient with osteopenia at baseline (T score of -1.9) developed osteoporosis during the treatment period (assessment by central review). The results for total hip BMD were similar, although the differences between the two treatments were less pronounced. During the 2 year period, fractures were reported by 4 of 103 patients (4%) in the letrozole arm, and 6 of 97 patients (6%) in the tamoxifen arm.

Lipid Study: In a safety trial in 263 postmenopausal women with resected receptor positive early breast cancer at 24 months comparing the effects on lipid profiles of adjuvant letrozole to tamoxifen, 12% of patients on letrozole had at least one total cholesterol value of a higher CTCAE grade than at baseline compared with 4% of patients on tamoxifen. In another postapproval randomized, multicenter, open label, study of letrozole vs anastrozole in the adjuvant treatment of postmenopausal women with hormone receptor and node positive breast cancer (FACE, NCT00248170), the median duration of treatment was 60 months for both treatment arms. Table 2 describes adverse reactions (Grades 1-4 and Grades 3-4) irrespective of relationship to study treatment in the adjuvant study (safety population).

Table 2: Adverse Reactions (CTC Grades 1-4), Occurring in at Least 5% of Patients in Either Treatment Arm, by Preferred Term (Safety set)
Adverse Reactions | Letrozole N = 2049 n (%) |  | Anastrozole N = 2062 n (%)
 | Grade 3/4 n (%) | All Grades n (%) | Grade 3/4 n (%) | All Grades n (%)
Patients with at least one AR | 628 (30.6) | 2049 (100.0) | 591 (28.7) | 2062 (100.0)
Arthralgia | 80 (3.9) | 987 (48.2) | 69 (3.3) | 987 (47.9)
Hot flush | 17 (0.8) | 666 (32.5) | 9 (0.4) | 666 (32.3)
Fatigue | 8 (0.4) | 345 (16.8) | 10 (0.5) | 343 (16.6)
Osteoporosis | 5 (0.2) | 223 (10.9) | 11 (0.5) | 225 (10.9)
Myalgia | 16 (0.8) | 233 (11.4) | 15 (0.7) | 212 (10.3)
Back pain | 11 (0.5) | 212 (10.3) | 17 (0.8) | 193 (9.4)
Osteopenia | 4 (0.2) | 203 (9.9) | 1 (0.0) | 173 (8.4)
Pain in extremity | 9 (0.4) | 168 (8.2) | 3 (0.1) | 174 (8.4)
Lymphoedema | 5 (0.2) | 159 (7.8) | 2 (0.1) | 179 (8.7)
Insomnia | 7 (0.3) | 160 (7.8) | 3 (0.1) | 149 (7.2)
Hypercholesterolaemia | 2 (0.1) | 155 (7.6) | 1 (0.0) | 151 (7.3)
Hypertension | 25 (1.2) | 156 (7.6) | 20 (1.0) | 149 (7.2)
Depression | 16 (0.8) | 147 (7.2) | 13 (0.6) | 137 (6.6)
Bone pain | 10 (0.5) | 138 (6.7) | 9 (0.4) | 122 (5.9)
Nausea | 6 (0.3) | 137 (6.7) | 5 (0.2) | 152 (7.4)
Headache | 3 (0.1) | 130 (6.3) | 5 (0.2) | 168 (8.1)
Alopecia | 2 (0.1) | 127 (6.2) | 0 (0.0) | 134 (6.5)
Musculoskeletal pain | 6 (0.3) | 123 (6.0) | 9 (0.4) | 147 (7.1)
Radiation skin injury | 11 (0.5) | 120 (5.9) | 6 (0.3) | 88 (4.3)
Dyspnea | 16 (0.8) | 118 (5.8) | 10 (0.5) | 96 (4.7)
Cough | 1 (0.0) | 106 (5.2) | 1 (0.0) | 120 (5.8)
Musculoskeletal stiffness | 2 (0.1) | 102 (5.0) | 2 (0.1) | 84 (4.1)
Dizziness | 2 (0.2) | 94 (4.6) | 7 (0.3) | 109 (5.3)

The following adverse reactions were also identified in less than 5% of the 2049 patients treated with letrozole and not included in the table: fall, vertigo, hyperbilirubinemia, jaundice, and chest pain.

Extended Adjuvant Treatment of Early Breast Cancer, Median Treatment Duration of 24 Months

In study MA-17, the median duration of extended adjuvant treatment was 24 months and the median duration of follow-up for safety was 28 months for patients receiving Femara and placebo.

Table 3 describes the adverse reactions occurring at a frequency of at least 5% in any treatment group during treatment. Most adverse reactions reported were Grade 1 and Grade 2 based on the CTC Version 2.0. In the extended adjuvant setting, the reported drug-related adverse reactions that were significantly different from placebo were hot flashes, arthralgia/arthritis, and myalgia.

Table 3: Adverse Reactions Occurring in at Least 5% of Patients in Either Treatment Arm
 | Number (%) of Patients with Grade 1-4 Adverse Reactions |  | Number (%) of Patients with Grade 3-4 Adverse Reactions
 | Femara | Placebo | Femara | Placebo
 | N = 2563 | N = 2573 | N = 2563 | N = 2573
Any Adverse Reactions | 2232 (87.1) | 2174 (84.5) | 419 (16.3) | 389 (15.1)
Vascular Disorders | 1375 (53.6) | 1230 (47.8) | 59 (2.3) | 74 (2.9)
Flushing | 1273 (49.7) | 1114 (43.3) | 3 (0.1) | 0
General Disorders | 1154 (45) | 1090 (42.4) | 30 (1.2) | 28 (1.1)
Asthenia | 862 (33.6) | 826 (32.1) | 16 (0.6) | 7 (0.3)
Edema NOS | 471 (18.4) | 416 (16.2) | 4 (0.2) | 3 (0.1)
Musculoskeletal Disorders | 978 (38.2) | 836 (32.5) | 71 (2.8) | 50 (1.9)
Arthralgia | 565 (22) | 465 (18.1) | 25 (1) | 20 (0.8)
Arthritis NOS | 173 (6.7) | 124 (4.8) | 10 (0.4) | 5 (0.2)
Myalgia | 171 (6.7) | 122 (4.7) | 8 (0.3) | 6 (0.2)
Back Pain | 129 (5) | 112 (4.4) | 8 (0.3) | 7 (0.3)
Nervous System Disorders | 863 (33.7) | 819 (31.8) | 65 (2.5) | 58 (2.3)
Headache | 516 (20.1) | 508 (19.7) | 18 (0.7) | 17 (0.7)
Dizziness | 363 (14.2) | 342 (13.3) | 9 (0.4) | 6 (0.2)
Skin Disorders | 830 (32.4) | 787 (30.6) | 17 (0.7) | 16 (0.6)
Sweating Increased | 619 (24.2) | 577 (22.4) | 1 (< 0.1) | 0
Gastrointestinal Disorders | 725 (28.3) | 731 (28.4) | 43 (1.7) | 42 (1.6)
Constipation | 290 (11.3) | 304 (11.8) | 6 (0.2) | 2 (< 0.1)
Nausea | 221 (8.6) | 212 (8.2) | 3 (0.1) | 10 (0.4)
Diarrhea NOS | 128 (5) | 143 (5.6) | 12 (0.5) | 8 (0.3)
Metabolic Disorders | 551 (21.5) | 537 (20.9) | 24 (0.9) | 32 (1.2)
Hypercholesterolemia | 401 (15.6) | 398 (15.5) | 2 (< 0.1) | 5 (0.2)
Reproductive Disorders | 303 (11.8) | 357 (13.9) | 9 (0.4) | 8 (0.3)
Vaginal Hemorrhage | 123 (4.8) | 171 (6.6) | 2 (< 0.1) | 5 (0.2)
Vulvovaginal Dryness | 137 (5.3) | 127 (4.9) | 0 | 0
Psychiatric Disorders | 320 (12.5) | 276 (10.7) | 21 (0.8) | 16 (0.6)
Insomnia | 149 (5.8) | 120 (4.7) | 2 (< 0.1) | 2 (< 0.1)
Respiratory Disorders | 279 (10.9) | 260 (10.1) | 30 (1.2) | 28 (1.1)
Dyspnea | 140 (5.5) | 137 (5.3) | 21 (0.8) | 18 (0.7)
Investigations | 184 (7.2) | 147 (5.7) | 13 (0.5) | 13 (0.5)
Infections and Infestations | 166 (6.5) | 163 (6.3) | 40 (1.6) | 33 (1.3)
Renal Disorders | 130 (5.1) | 100 (3.9) | 12 (0.5) | 6 (0.2)

Based on a median follow-up of patients for 28 months, the incidence of clinical fractures from the core randomized study in patients who received Femara was 5.9% (152) and placebo was 5.5% (142). The incidence of self-reported osteoporosis was higher in patients who received Femara 6.9% (176) than in patients who received placebo 5.5% (141). Bisphosphonates were administered to 21.1% of the patients who received Femara and 18.7% of the patients who received placebo.

The incidence of cardiovascular ischemic events from the core randomized study was comparable between patients who received Femara 6.8% (175) and placebo 6.5% (167).

A patient-reported measure that captures treatment impact on important symptoms associated with estrogen deficiency demonstrated a difference in favor of placebo for vasomotor and sexual symptom domains.

Bone Substudy: [see Warnings and Precautions (5.1)]

Lipid Substudy: In the extended adjuvant setting, based on a median duration of follow-up of 62 months, there was no significant difference between Femara and placebo in total cholesterol or in any lipid fraction at any time over 5 years. Use of lipid lowering drugs or dietary management of elevated lipids was allowed [see Warnings and Precautions (5.2)].

Updated Analysis, Extended Adjuvant Treatment of Early Breast Cancer, Median Treatment Duration of 60 Months

The extended adjuvant treatment trial (MA-17) was unblinded early [see Adverse Reactions (6)]. At the updated (final analysis), overall the side effects seen were consistent to those seen at a median treatment duration of 24 months.

During treatment or within 30 days of stopping treatment (median duration of treatment 60 months) a higher rate of fractures was observed for Femara (10.4%) compared to placebo (5.8%), as also a higher rate of osteoporosis (Femara 12.2% vs placebo 6.4%).

Based on 62 months median duration of follow-up in the randomized letrozole arm in the safety population the incidence of new fractures at any time after randomization was 13.3% for letrozole and 7.8% for placebo. The incidence of new osteoporosis was 14.5% for letrozole and 7.8% for placebo.

During treatment or within 30 days of stopping treatment (median duration of treatment 60 months), the incidence of cardiovascular events was 9.8% for Femara and 7.0% for placebo.

Based on 62 months median duration of follow-up in the randomized letrozole arm in the safety population the incidence of cardiovascular disease at any time after randomization was 14.4% for letrozole and 9.8% for placebo.

Lipid Substudy: In the extended adjuvant setting (MA-17), based on a median duration of follow-up of 62 months, there was no significant difference between Femara and placebo in total cholesterol or in any lipid fraction over 5 years. Use of lipid lowering drugs or dietary management of elevated lipids was allowed [see Warnings and Precautions (5.2)].

First-Line Treatment of Advanced Breast Cancer

In study P025 a total of 455 patients were treated for a median time of exposure of 11 months in the Femara arm (median 6 months in the tamoxifen arm). The incidence of adverse reactions was similar for Femara and tamoxifen. The most frequently reported adverse reactions were bone pain, hot flushes, back pain, nausea, arthralgia, and dyspnea. Discontinuations for adverse reactions other than progression of tumor occurred in 10/455 (2%) of patients on Femara and in 15/455 (3%) of patients on tamoxifen.

Adverse reactions that were reported in at least 5% of the patients treated with Femara 2.5 mg or tamoxifen 20 mg in the first-line treatment study are shown in Table 4.

Table 4: Adverse Reactions Occurring in at Least 5% of Patients in Either Treatment Arm
Adverse Reactions | Femara | Tamoxifen
 | 2.5 mg | 20 mg
 | (N = 455) | (N = 455)
 | % | %
General Disorders
Fatigue | 13 | 13
Chest Pain | 8 | 9
Edema Peripheral | 5 | 6
Pain NOS | 5 | 7
Weakness | 6 | 4
Investigations
Weight Decreased | 7 | 5
Vascular Disorders
Hot Flushes | 19 | 16
Hypertension | 8 | 4
Gastrointestinal Disorders
Nausea | 17 | 17
Constipation | 10 | 11
Diarrhea | 8 | 4
Vomiting | 7 | 8
Infections/Infestations
Influenza | 6 | 4
Urinary Tract Infection NOS | 6 | 3
Injury, Poisoning and Procedural Complications
Post-Mastectomy Lymphedema | 7 | 7
Metabolism and Nutrition Disorders
Anorexia | 4 | 6
Musculoskeletal and Connective Tissue Disorders
Bone Pain | 22 | 21
Back Pain | 18 | 19
Arthralgia | 16 | 15
Pain in Limb | 10 | 8
Nervous System Disorders
Headache NOS | 8 | 7
Psychiatric Disorders
Insomnia | 7 | 4
Reproductive System and Breast Disorders
Breast Pain | 7 | 7
Respiratory, Thoracic and Mediastinal Disorders
Dyspnea | 18 | 17
Cough | 13 | 13
Chest Wall Pain | 6 | 6

Other less frequent (less than or equal to 2%) adverse reactions considered consequential for both treatment groups, included peripheral thromboembolic events, cardiovascular events, and cerebrovascular events. Peripheral thromboembolic events included venous thrombosis, thrombophlebitis, portal vein thrombosis, and pulmonary embolism. Cardiovascular events included angina, myocardial infarction, myocardial ischemia, and coronary heart disease. Cerebrovascular events included transient ischemic attacks, thrombotic or hemorrhagic strokes, and development of hemiparesis.

Second-Line Treatment of Advanced Breast Cancer

Study discontinuations in the megestrol acetate comparison study (AR/BC2) for adverse reactions other than progression of tumor were 5/188 (2.7%) on Femara 0.5 mg, in 4/174 (2.3%) on Femara 2.5 mg, and in 15/190 (7.9%) on megestrol acetate. There were fewer thromboembolic events at both Femara doses than on the megestrol acetate arm (0.6% vs 4.7%). There was also less vaginal bleeding (0.3% vs 3.2%) on Femara than on megestrol acetate. In the aminoglutethimide comparison study (AR/BC3), discontinuations for reasons other than progression occurred in 6/193 (3.1%) on 0.5 mg Femara, 7/185 (3.8%) on 2.5 mg Femara, and 7/178 (3.9%) of patients on aminoglutethimide.

Comparisons of the incidence of adverse reactions revealed no significant differences between the high and low dose Femara groups in either study. Most of the adverse reactions observed in all treatment groups were mild to moderate in severity and it was generally not possible to distinguish adverse reactions due to treatment from the consequences of the patient’s metastatic breast cancer, the effects of estrogen deprivation, or intercurrent illness.

Adverse reactions that were reported in at least 5% of the patients treated with Femara 0.5 mg, Femara 2.5 mg, megestrol acetate, or aminoglutethimide in the two controlled trials AR/BC2 and AR/BC3 are shown in Table 5.

Table 5: Adverse Reactions Occurring at a Frequency of at Least 5% of Patients in Either Treatment Arm
Adverse Reactions | Pooled | Pooled | Megestrol
 | Femara | Femara | Acetate | Aminoglutethimide
 | 2.5 mg | 0.5 mg | 160 mg | 500 mg
 | (N = 359) | (N = 380) | (N = 189) | (N = 178)
 | % | % | % | %
Body as a Whole
Chest Pain | 6 | 3 | 7 | 3
Peripheral Edema^1 | 5 | 5 | 8 | 3
Asthenia | 4 | 5 | 4 | 5
Weight Increase | 2 | 2 | 9 | 3
Cardiovascular
Hypertension | 5 | 7 | 5 | 6
Digestive System
Nausea | 13 | 15 | 9 | 14
Vomiting | 7 | 7 | 5 | 9
Constipation | 6 | 7 | 9 | 7
Diarrhea | 6 | 5 | 3 | 4
Pain-Abdominal | 6 | 5 | 9 | 8
Anorexia | 5 | 3 | 5 | 5
Dyspepsia | 3 | 4 | 6 | 5
Infections/Infestations
Viral Infection | 6 | 5 | 6 | 3
Lab Abnormality
Hypercholesterolemia | 3 | 3 | 0 | 6
Musculoskeletal System
Musculoskeletal^2 | 21 | 22 | 30 | 14
Arthralgia | 8 | 8 | 8 | 3
Nervous System
Headache | 9 | 12 | 9 | 7
Somnolence | 3 | 2 | 2 | 9
Dizziness | 3 | 5 | 7 | 3
Respiratory System
Dyspnea | 7 | 9 | 16 | 5
Coughing | 6 | 5 | 7 | 5
Skin and Appendages
Hot Flushes | 6 | 5 | 4 | 3
Rash^3 | 5 | 4 | 3 | 12
Pruritus | 1 | 2 | 5 | 3
^1Includes peripheral edema, leg edema, dependent edema, edema.
^2Includes musculoskeletal pain, skeletal pain, back pain, arm pain, leg pain.
^3Includes rash, erythematous rash, maculopapular rash, psoriasiform rash, vesicular rash.

Other less frequent (less than 5%) adverse reactions considered consequential and reported in at least 3 patients treated with Femara, included hypercalcemia, fracture, depression, anxiety, pleural effusion, alopecia, increased sweating, and vertigo.

First and Second-Line Treatment of Advanced Breast Cancer

In the combined analysis of the first- and second-line metastatic trials and postmarketing experiences other adverse reactions that were reported were cataract, eye irritation, palpitations, cardiac failure, tachycardia, dysesthesia (including hypesthesia/paresthesia), arterial thrombosis, memory impairment, irritability, nervousness, urticaria, increased urinary frequency, leukopenia, stomatitis cancer pain, pyrexia, vaginal discharge, appetite increase, dryness of skin and mucosa (including dry mouth), and disturbances of taste and thirst.

6.2 Postmarketing Experience

The following adverse reactions have been identified during postapproval use of Femara. Because these reactions are reported voluntarily from a population of uncertain size, it is not always possible to reliably estimate their frequency or establish a causal relationship to drug exposure.

- Eye Disorders: blurred vision
- Hepatobiliary Disorders: increased hepatic enzymes, hepatitis
- Immune System Disorders: anaphylactic reactions, hypersensitivity reactions
- Nervous System Disorders: carpal tunnel syndrome
- Pregnancy: spontaneous abortions, congenital birth defects
- Skin and subcutaneous disorders: angioedema, toxic epidermal necrolysis, erythema multiforme
- Musculoskeletal and connective tissue disorders: tendon disorders including tendon rupture, tendonitis, tenosynovitis, and tenosynovitis stenosans (trigger finger)

7 DRUG INTERACTIONS

Tamoxifen

Coadministration of Femara and tamoxifen 20 mg daily resulted in a reduction of letrozole plasma levels of 38% on average (Study P015). Clinical experience in the second-line breast cancer trials (AR/BC2 and AR/BC3) indicates that the therapeutic effect of Femara therapy is not impaired if Femara is administered immediately after tamoxifen.

Cimetidine

A pharmacokinetic interaction study with cimetidine (Study P004) showed no clinically significant effect on letrozole pharmacokinetics.

Warfarin

An interaction study (P017) with warfarin showed no clinically significant effect of letrozole on warfarin pharmacokinetics.

Other Anticancer Agents

There is no clinical experience to date on the use of Femara in combination with other anticancer agents.

8 USE IN SPECIFIC POPULATIONS

8.1 Pregnancy

Risk Summary

Based on postmarketing reports, findings from animal studies and the mechanism of action, Femara can cause fetal harm and is contraindicated for use in pregnant women. In post-marketing reports, use of letrozole during pregnancy resulted in cases of spontaneous abortions and congenital birth defects; however, the data are insufficient to inform a drug-associated risk [see Contraindications (4), Warnings and Precautions (5.6), Adverse Reactions (6.2), and Clinical Pharmacology (12.1)].

In animal reproduction studies, administration of letrozole to pregnant animals during organogenesis resulted in increased post-implantation pregnancy loss and resorption, fewer live fetuses, and fetal malformation affecting the renal and skeletal systems in rats and rabbits at doses approximately 0.1 times the daily maximum recommended human dose (MRHD) on a mg/m^2 basis (see Data).

The background risk of major birth defects and miscarriage for the indicated population is unknown. However, the background risk in the U.S. general population of major birth defects is 2% to 4% and of miscarriage is 15% to 20% of clinically recognized pregnancies.

Data

Animal Data

In a fertility and early embryonic development toxicity study in female rats, oral administration of letrozole starting 2 weeks before mating until pregnancy day 6 resulted in an increase in pre-implantation loss at doses ≥ 0.003 mg/kg/day (approximately 0.01 times the maximum recommended human dose on a mg/m^2 basis).

In an embryo-fetal developmental toxicity study in rats, daily administration of oral letrozole during the period of organogenesis at doses ≥ 0.003 mg/kg (approximately 0.01 time the maximum recommended human dose on a mg/m^2 basis) resulted in embryo-fetal toxicity including intrauterine mortality, increased resorptions and postimplantation loss, decreased numbers of live fetuses and fetal anomalies, including absence and shortening of renal papilla, dilation of ureter, edema, and incomplete ossification of frontal skull and metatarsals. Letrozole was teratogenic to rats at a dose of 0.03 mg/kg (approximately 0.01 times the maximum recommended human dose on a mg/m^2 basis) and caused fetal domed head and cervical/centrum vertebral fusion.

In the embryo-fetal development toxicity study in rabbits, daily administration of oral letrozole during the period of organogenesis at doses ≥ 0.002 mg/kg (approximately 0.01 times the maximum recommended human dose on a mg/m^2 basis) resulted in embryo-fetal toxicity, including intrauterine mortality, increased resorption, increased postimplantation loss and decreased numbers of live fetuses. Fetal anomalies included incomplete ossification of the skull, sternebrae, and fore- and hind legs.

8.2 Lactation

Risk Summary

It is not known if letrozole is present in human milk. There are no data on the effects of letrozole on the breastfed infant or milk production. Exposure of lactating rats to letrozole was associated with impaired reproductive performance of the male offspring (see Data). Because of the potential for serious adverse reactions in breastfed infants from Femara, advise lactating women not to breastfeed while taking Femara and for at least 3 weeks after the last dose.

Data

Animal Data

In a postnatal developmental toxicity study in lactating rats, letrozole was administered orally at doses of 1, 0.003, 0.03, or 0.3 mg/kg/day on Day 0 through Day 20 of lactation. The reproductive performance of the male offspring was impaired at letrozole dose as low as 0.003 mg/kg/day (approximately 0.01 times the maximum recommended human dose on a mg/m^2 basis), as reflected by decreased mating and pregnancy ratios. There were no effects on the reproductive performance of female offspring.

8.3 Females and Males of Reproductive Potential

Pregnancy Testing

Based on animal studies, Femara can cause fetal harm when administered to a pregnant woman [see Use in Specific Populations (8.1)]. Females of reproductive potential should have a pregnancy test prior to starting treatment with Femara.

Contraception

Females

Based on animal studies, Femara can cause fetal harm when administered to a pregnant woman [see Use in Specific Populations (8.1)]. Advise females of reproductive potential to use effective contraception during treatment with Femara and for at least 3 weeks after the last dose.

Infertility

Females

Based on studies in female animals, Femara may impair fertility in females of reproductive potential [see Nonclinical Toxicology (13.1)].

Males

Based on studies in male animals, Femara may impair fertility in males of reproductive potential [see Nonclinical Toxicology (13.1)].

8.4 Pediatric Use

The safety and effectiveness in pediatric patients have not been established.

Letrozole administration to young (postnatal day 7) rats for 12 weeks duration at 0.003, 0.03, 0.3 mg/kg/day by oral gavage resulted in adverse skeletal/growth effects (bone maturation, bone mineral density) and neuroendocrine and reproductive developmental perturbations of the hypothalamic-pituitary axis. Administration of 0.3 mg/kg/day resulted in AUC values that were similar to the AUC in adult patients receiving the recommended dose of 2.5 mg/day. Decreased fertility was accompanied by hypertrophy of the hypophysis and testicular changes that included degeneration of the seminiferous tubular epithelium and atrophy of the female reproductive tract. Young rats in this study were allowed to recover following discontinuation of letrozole treatment for 42 days. Histopathological changes were not reversible at clinically relevant exposures.

8.5 Geriatric Use

The median age of patients in all studies of first-line and second-line treatment of metastatic breast cancer was 64-65 years. About 1/3 of the patients were greater than or equal to 70 years old. In the first-line study, patients greater than or equal to 70 years of age experienced longer time to tumor progression and higher response rates than patients less than 70.

For the extended adjuvant setting (MA-17), more than 5,100 postmenopausal women were enrolled in the clinical study. In total, 41% of patients were aged 65 years or older at enrollment, while 12% were 75 or older. In the extended adjuvant setting, no overall differences in safety or efficacy were observed between these older patients and younger patients, and other reported clinical experience has not identified differences in responses between the elderly and younger patients, but greater sensitivity of some older individuals cannot be ruled out.

In the adjuvant setting (BIG 1-98), more than 8,000 postmenopausal women were enrolled in the clinical study. In total, 36% of patients were aged 65 years or older at enrollment, while 12% were 75 or older. More adverse reactions were generally reported in elderly patients irrespective of study treatment allocation. However, in comparison to tamoxifen, no overall differences with regards to the safety and efficacy profiles were observed between elderly patients and younger patients.

10 OVERDOSAGE

Isolated cases of Femara overdose have been reported. In these instances, the highest single dose ingested was 62.5 mg or 25 tablets. While no serious adverse reactions were reported in these cases, because of the limited data available, no firm recommendations for treatment can be made. However, emesis could be induced if the patient is alert. In general, supportive care and frequent monitoring of vital signs are also appropriate. In single-dose studies, the highest dose used was 30 mg, which was well tolerated; in multiple-dose trials, the largest dose of 10 mg was well tolerated.

Lethality was observed in mice and rats following single oral doses that were equal to or greater than 2,000 mg/kg (about 4,000 to 8,000 times the daily maximum recommended human dose on a mg/m^2 basis); death was associated with reduced motor activity, ataxia and dyspnea. Lethality was observed in cats following single IV doses that were equal to or greater than 10 mg/kg (about 50 times the daily maximum recommended human dose on a mg/m^2 basis); death was preceded by depressed blood pressure and arrhythmias.

11 DESCRIPTION

Femara tablets for oral administration contains 2.5 mg of letrozole, a nonsteroidal aromatase inhibitor (inhibitor of estrogen synthesis). It is chemically described as 4,4'-(1H-1,2,4-Triazol-1-ylmethylene) dibenzonitrile, and its structural formula is

Letrozole is a white to yellowish crystalline powder, practically odorless, freely soluble in dichloromethane, slightly soluble in ethanol, and practically insoluble in water. It has a molecular weight of 285.31 g/mol, empirical formula C17H11N5, and a melting range of 184°C to 185°C.

Femara is available as 2.5 mg tablets for oral administration.

Inactive Ingredients: Colloidal silicon dioxide, ferric oxide, hydroxypropyl methylcellulose, lactose monohydrate, magnesium stearate, maize starch, microcrystalline cellulose, polyethylene glycol, sodium starch glycolate, talc, and titanium dioxide.

12 CLINICAL PHARMACOLOGY

12.1 Mechanism of Action

The growth of some cancers of the breast is stimulated or maintained by estrogens. Treatment of breast cancer thought to be hormonally responsive (i.e., estrogen and/or progesterone receptor positive or receptor unknown) has included a variety of efforts to decrease estrogen levels (ovariectomy, adrenalectomy, hypophysectomy) or inhibit estrogen effects (antiestrogens and progestational agents). These interventions lead to decreased tumor mass or delayed progression of tumor growth in some women.

In postmenopausal women, estrogens are mainly derived from the action of the aromatase enzyme, which converts adrenal androgens (primarily androstenedione and testosterone) to estrone and estradiol. The suppression of estrogen biosynthesis in peripheral tissues and in the cancer tissue itself can therefore be achieved by specifically inhibiting the aromatase enzyme.

Letrozole is a nonsteroidal competitive inhibitor of the aromatase enzyme system; it inhibits the conversion of androgens to estrogens. In adult nontumor- and tumor-bearing female animals, letrozole is as effective as ovariectomy in reducing uterine weight, elevating serum LH, and causing the regression of estrogen-dependent tumors. In contrast to ovariectomy, treatment with letrozole does not lead to an increase in serum FSH. Letrozole selectively inhibits gonadal steroidogenesis but has no significant effect on adrenal mineralocorticoid or glucocorticoid synthesis.

Letrozole inhibits the aromatase enzyme by competitively binding to the heme of the cytochrome P450 subunit of the enzyme, resulting in a reduction of estrogen biosynthesis in all tissues. Treatment of women with letrozole significantly lowers serum estrone, estradiol and estrone sulfate and has not been shown to significantly affect adrenal corticosteroid synthesis, aldosterone synthesis, or synthesis of thyroid hormones.

12.2 Pharmacodynamics

In postmenopausal patients with advanced breast cancer, daily doses of 0.1 mg to 5 mg Femara (letrozole) suppress plasma concentrations of estradiol, estrone, and estrone sulfate by 75% to 95% from baseline with maximal suppression achieved within two-three days. Suppression is dose-related, with doses of 0.5 mg and higher giving many values of estrone and estrone sulfate that were below the limit of detection in the assays. Estrogen suppression was maintained throughout treatment in all patients treated at 0.5 mg or higher.

Letrozole is highly specific in inhibiting aromatase activity. There is no impairment of adrenal steroidogenesis. No clinically-relevant changes were found in the plasma concentrations of cortisol, aldosterone, 11-deoxycortisol, 17-hydroxy-progesterone, ACTH or in plasma renin activity among postmenopausal patients treated with a daily dose of Femara 0.1 mg to 5 mg. The ACTH stimulation test performed after 6 and 12 weeks of treatment with daily doses of 0.1, 0.25, 0.5, 1, 2.5, and 5 mg did not indicate any attenuation of aldosterone or cortisol production. Glucocorticoid or mineralocorticoid supplementation is, therefore, not necessary.

No changes were noted in plasma concentrations of androgens (androstenedione and testosterone) among healthy postmenopausal women after 0.1, 0.5, and 2.5 mg single doses of Femara or in plasma concentrations of androstenedione among postmenopausal patients treated with daily doses of 0.1 mg to 5 mg. This indicates that the blockade of estrogen biosynthesis does not lead to accumulation of androgenic precursors. Plasma levels of LH and FSH were not affected by letrozole in patients, nor was thyroid function as evaluated by TSH levels, T3 uptake, and T4 levels.

12.3 Pharmacokinetics

Absorption and Distribution: Letrozole is rapidly and completely absorbed from the gastrointestinal tract and absorption is not affected by food. It is metabolized slowly to an inactive metabolite whose glucuronide conjugate is excreted renally, representing the major clearance pathway. About 90% of radiolabeled letrozole is recovered in urine. Letrozole’s terminal elimination half-life is about 2 days and steady-state plasma concentration after daily 2.5 mg dosing is reached in 2-6 weeks. Plasma concentrations at steady state are 1.5 to 2 times higher than predicted from the concentrations measured after a single dose, indicating a slight non-linearity in the pharmacokinetics of letrozole upon daily administration of 2.5 mg. These steady-state levels are maintained over extended periods, however, and continuous accumulation of letrozole does not occur. Letrozole is weakly protein bound and has a large volume of distribution (approximately 1.9 L/kg).

Elimination

Metabolism and Excretion: Metabolism to a pharmacologically-inactive carbinol metabolite (4,4'-methanol-bisbenzonitrile) and renal excretion of the glucuronide conjugate of this metabolite is the major pathway of letrozole clearance. Of the radiolabel recovered in urine, at least 75% was the glucuronide of the carbinol metabolite, about 9% was two unidentified metabolites, and 6% was unchanged letrozole.

In human microsomes with specific CYP isozyme activity, CYP3A4 metabolized letrozole to the carbinol metabolite while CYP2A6 formed both this metabolite and its ketone analog. In human liver microsomes, letrozole inhibited CYP2A6 and CYP2C19, however, the clinical significance of these findings is unknown.

Specific Populations

Pediatric, Geriatric and Race: In the study populations (adults ranging in age from 35 to greater than 80 years), no change in pharmacokinetic parameters was observed with increasing age. Differences in letrozole pharmacokinetics between adult and pediatric populations have not been studied. Differences in letrozole pharmacokinetics due to race have not been studied.

Renal Impairment: In a study of volunteers with varying renal function (24-hour creatinine clearance: 9 to 116 mL/min), no effect of renal function on the pharmacokinetics of single doses of 2.5 mg of Femara was found. In addition, in a study (AR/BC2) of 347 patients with advanced breast cancer, about half of whom received 2.5 mg Femara and half 0.5 mg Femara, renal impairment (calculated creatinine clearance: 20 to 50 mL/min) did not affect steady-state plasma letrozole concentrations.

Hepatic Impairment: In a study of subjects with mild to moderate non-metastatic hepatic dysfunction (e.g., cirrhosis, Child-Pugh classification A and B), the mean area under curve (AUC) values of the volunteers with moderate hepatic impairment were 37% higher than in normal subjects, but still within the range seen in subjects without impaired function.

In a pharmacokinetic study, subjects with liver cirrhosis and severe hepatic impairment (Child-Pugh classification C, which included bilirubins about 2-11 times ULN with minimal to severe ascites) had two-fold increase in exposure (AUC) and 47% reduction in systemic clearance. Breast cancer patients with severe hepatic impairment are thus expected to be exposed to higher levels of letrozole than patients with normal liver function receiving similar doses of this drug [see Dosage and Administration (2.5)].

13 NONCLINICAL TOXICOLOGY

13.1 Carcinogenesis, Mutagenesis, Impairment of Fertility

A conventional carcinogenesis study in mice at doses of 0.6 to 60 mg/kg/day (about 1 to 100 times the daily maximum recommended human dose on a mg/m^2 basis) administered by oral gavage for up to 2 years revealed a dose-related increase in the incidence of benign ovarian stromal tumors. The incidence of combined hepatocellular adenoma and carcinoma showed a significant trend in females when the high dose group was excluded due to low survival. In a separate study, plasma AUC0-12hr levels in mice at 60 mg/kg/day were 55 times higher than the AUC0-24hr level in breast cancer patients at the recommended dose. The carcinogenicity study in rats at oral doses of 0.1 to 10 mg/kg/day (about 0.4 to 40 times the daily maximum recommended human dose on a mg/m^2 basis) for up to 2 years also produced an increase in the incidence of benign ovarian stromal tumors at 10 mg/kg/day. Ovarian hyperplasia was observed in females at doses equal to or greater than 0.1 mg/kg/day. At 10 mg/kg/day, plasma AUC0-24hr levels in rats were 80 times higher than the level in breast cancer patients at the recommended dose. The benign ovarian stromal tumors observed in mice and rats were considered to be related to the pharmacological inhibition of estrogen synthesis and may be due to increased luteinizing hormone resulting from the decrease in circulating estrogen.

Femara (letrozole) was not mutagenic in in vitro tests (Ames and E.coli bacterial tests) but was observed to be a potential clastogen in in vitro assays (CHO K1 and CCL 61 Chinese hamster ovary cells). Letrozole was not clastogenic in vivo (micronucleus test in rats).

In a fertility and early embryonic development toxicity study in female rats, oral administration of letrozole starting 2 weeks before mating until pregnancy day 6 resulted in an increase in pre-implantation loss at doses ≥ 0.03 mg/kg/day (approximately 0.1 times the maximum recommended human dose on a mg/m^2 basis). In repeat-dose toxicity studies, administration of letrozole caused sexual inactivity in females and atrophy of the reproductive tract in males and females at doses of 0.6, 0.1 and 0.03 mg/kg in mice, rats and dogs, respectively (approximately 1, 0.4, and 0.4 times the daily maximum recommended human dose on a mg/m^2 basis, respectively).

14 CLINICAL STUDIES

14.1 Updated Adjuvant Treatment of Early Breast Cancer

In a multicenter study (BIG 1-98, NCT00004205) enrolling over 8,000 postmenopausal women with resected, receptor-positive early breast cancer, one of the following treatments was randomized in a double-blind manner:

Option 1:

1. Tamoxifen for 5 years
2. Femara for 5 years
3. Tamoxifen for 2 years followed by Femara for 3 years
4. Femara for 2 years followed by tamoxifen for 3 years

Option 2:

A. Tamoxifen for 5 years

B. Femara for 5 years

The study in the adjuvant setting, BIG 1-98 was designed to answer two primary questions: whether Femara for 5 years was superior to Tamoxifen for 5 years (Primary Core Analysis) and whether switching endocrine treatments at 2 years was superior to continuing the same agent for a total of 5 years (Sequential Treatments Analysis). Selected baseline characteristics for the study population are shown in Table 6.

The primary endpoint of this trial was DFS (i.e., interval between randomization and earliest occurrence of a local, regional, or distant recurrence, or invasive contralateral breast cancer, or death from any cause). The secondary endpoints were overall survival (OS), systemic disease-free survival (SDFS), invasive contralateral breast cancer, time to breast cancer recurrence (TBR) and time to distant metastasis (TDM).

The Primary Core Analysis (PCA) included all patients and all follow-up in the monotherapy arms in both randomization options, but follow-up in the two sequential treatments arms was truncated 30 days after switching treatments. The PCA was conducted at a median treatment duration of 24 months and a median follow-up of 26 months. Femara was superior to tamoxifen in all endpoints except overall survival and contralateral breast cancer [e.g., DFS: hazard ratio (HR) 0.79; 95% CI (0.68, 0.92); P = 0.002; SDFS: HR 0.83; 95% CI (0.70, 0.97); TDM: HR 0.73; 95% CI (0.60, 0.88); OS: HR 0.86; 95% CI (0.70, 1.06).

In 2005, based on recommendations by the independent Data Monitoring Committee, the tamoxifen arms were unblinded and patients were allowed to complete initial adjuvant therapy with Femara (if they had received tamoxifen for at least 2 years) or to start extended adjuvant treatment with Femara (if they had received tamoxifen for at least 4.5 years) if they remained alive and disease-free. In total, 632 patients crossed to Femara or another aromatase inhibitor. Approximately 70% (448) of these 632 patients crossed to Femara to complete initial adjuvant therapy and most of these crossed in years 3 to 4. All of these patients were in Option 1. A total of 184 patients started extended adjuvant therapy with Femara (172 patients) or with another aromatase inhibitor (12 patients). To explore the impact of this selective crossover, results from analyses censoring follow-up at the date of the selective crossover (in the tamoxifen arm) are presented for the MAA.

The PCA allowed the results of Femara for 5 years compared with tamoxifen for 5 years to be reported in 2005 after a median follow-up of only 26 months. The design of the PCA is not optimal to evaluate the effect of Femara after a longer time (because follow-up was truncated in two arms at around 25 months). The MAA (ignoring the two sequential treatment arms) provided follow-up equally as long in each treatment and did not over-emphasize early recurrences as the PCA did. The MAA thus provides the clinically appropriate updated efficacy results in answer to the first primary question, despite the confounding of the tamoxifen reference arm by the selective crossover to Femara. The updated results for the MAA are summarized in Table 7. Median follow-up for this analysis is 73 months.

The Sequential Treatments Analysis (STA) addresses the second primary question of the study. The primary analysis for the STA was from switch (or equivalent time-point in monotherapy arms) + 30 days (STA-S) with a two-sided test applied to each pair-wise comparison at the 2.5% level. Additional analyses were conducted from randomization (STA-R) but these comparisons (added in light of changing medical practice) were under-powered for efficacy.

Table 6: Adjuvant Study - Patient and Disease Characteristics (ITT Population)
 | Primary Core Analysis (PCA) |  | Monotherapy Arms Analysis (MAA)
 | Femara | Tamoxifen | Femara | Tamoxifen
 | N = 4003 | N = 4007 | N = 2463 | N = 2459
Characteristic | n (%) | n (%) | n (%) | n (%)
Age (median, years) | 61 | 61 | 61 | 61
Age range (years) | 38-89 | 39-90 | 38-88 | 39-90
Hormone receptor status (%)
ER+ and/or PgR+ | 99.7 | 99.7 | 99.7 | 99.7
Both unknown | 0.3 | 0.3 | 0.3 | 0.3
Nodal status (%)
Node negative | 52 | 52 | 50 | 52
Node positive | 41 | 41 | 43 | 41
Nodal status unknown | 7 | 7 | 7 | 7
Prior adjuvant chemotherapy (%) | 24 | 24 | 24 | 24

Table 7: Updated Adjuvant Study Results - Monotherapy Arms Analysis (Median Follow-up 73 Months)
 |  | Femara N = 2463 |  | Tamoxifen N = 2459 |  | Hazard ratio
 |  | Events (%) | 5-year rate | Events (%) | 5-year rate | (95% CI) | P
Disease-free survival^1 | ITT | 445 (18.1) | 87.4 | 500 (20.3) | 84.7 | 0.87 (0.76, 0.99) |  | 0.03
 | Censor | 445 | 87.4 | 483 | 84.2 | 0.84 (0.73, 0.95)
0 positive nodes | ITT | 165 | 92.2 | 189 | 90.3 | 0.88 (0.72, 1.09)
1-3 positive nodes | ITT | 151 | 85.6 | 163 | 83.0 | 0.85 (0.68, 1.06)
>=4 positive nodes | ITT | 123 | 71.2 | 142 | 62.6 | 0.81 (0.64, 1.03)
Adjuvant chemotherapy | ITT | 119 | 86.4 | 150 | 80.6 | 0.77 (0.60, 0.98)
No chemotherapy | ITT | 326 | 87.8 | 350 | 86.1 | 0.91 (0.78, 1.06)
Systemic DFS^2 | ITT | 401 | 88.5 | 446 | 86.6 | 0.88 (0.77,1.01)
Time to distant metastasis^3 | ITT | 257 | 92.4 | 298 | 90.1 | 0.85 (0.72, 1.00)
Adjuvant chemotherapy | ITT | 84 | - | 109 | - | 0.75 (0.56-1.00)
No chemotherapy | ITT | 173 | - | 189 | - | 0.90 (0.73,1.11)
Distant DFS^4 | ITT | 385 | 89.0 | 432 | 87.1 | 0.87 (0.76,1.00)
Contralateral breast cancer | ITT | 34 | 99.2 | 44 | 98.6 | 0.76 (0.49, 1.19)
Overall survival | ITT | 303 | 91.8 | 343 | 90.9 | 0.87 (0.75, 1.02)
 | Censor | 303 | 91.8 | 338 | 90.1 | 0.82 (0.70, 0.96)
0 positive nodes | ITT | 107 | 95.2 | 121 | 94.8 | 0.90 (0.69.1.16)
1-3 positive nodes | ITT | 99 | 90.8 | 114 | 90.6 | 0.81(0.62,1.06)
> = 4 positive nodes | ITT | 92 | 80.2 | 104 | 73.6 | 0.86 (0.65, 1.14)
Adjuvant chemotherapy | ITT | 76 | 91.5 | 96 | 88.4 | 0.79 (0.58, 1.06)
No chemotherapy | ITT | 227 | 91.9 | 247 | 91.8 | 0.91 (0.76, 1.08)
Definition of:
^1Disease-free survival: Interval from randomization to earliest event of invasive loco-regional recurrence, distant metastasis, invasive contralateral breast cancer, or death without a prior event.
^2Systemic disease-free survival: Interval from randomization to invasive regional recurrence, distant metastasis, or death without a prior cancer event.
^3Time to distant metastasis: Interval from randomization to distant metastasis.
^4Distant disease-free survival: Interval from randomization to earlier event of relapse in a distant site or death from any cause.
ITT analysis ignores selective crossover in tamoxifen arms.
Censored analysis censors follow-up at the date of selective crossover in 632 patients who crossed to Femara or another aromatase inhibitor after the tamoxifen arms were unblinded in 2005.

Figure 1 shows the Kaplan-Meier curves for Disease-Free Survival Monotherapy Analysis.

Figure 1: Disease-Free Survival (Median follow-up 73 months, ITT Approach)

DFS events defined as loco-regional recurrence, distant metastasis, invasive contralateral breast cancer, or death from any cause (i.e., definition excludes second non-breast primary cancers).

The medians of overall survival for both arms were not reached for the MAA. There was no statistically significant difference in overall survival. The hazard ratio for survival in the Femara arm compared to the tamoxifen arm was 0.87, with 95% CI (0.75, 1.02) (see Table 7).

There were no significant differences in DFS, OS, SDFS, and Distant DFS from switch in the Sequential Treatments Analysis with respect to either monotherapy (e.g., [tamoxifen 2 years followed by] Femara 3 years versus tamoxifen beyond 2 years, DFS HR 0.89; 97.5% CI 0.68, 1.15 and [Femara 2 years followed by] tamoxifen 3 years versus Femara beyond 2 years, DFS HR 0.93; 97.5% CI 0.71, 1.22).

There were no significant differences in DFS, OS, SDFS, and Distant DFS from randomization in the Sequential Treatments Analyses.

14.2 Extended Adjuvant Treatment of Early Breast Cancer, Median Treatment Duration of 24 Months

A double-blind, randomized, placebo-controlled trial (MA-17, NCT00003140) of Femara was performed in over 5,100 postmenopausal women with receptor-positive or unknown primary breast cancer who were disease free after 5 years of adjuvant treatment with tamoxifen.

The planned duration of treatment for patients in the study was 5 years, but the trial was terminated early because of an interim analysis showing a favorable Femara effect on time without recurrence or contralateral breast cancer. At the time of unblinding, women had been followed for a median of 28 months, 30% of patients had completed 3 or more years of follow-up and less than 1% of patients had completed 5 years of follow-up.

Selected baseline characteristics for the study population are shown in Table 8.

Table 8: Selected Study Population Demographics (Modified ITT Population)
Baseline Status | Femara | Placebo
 | N = 2582 | N = 2586
Hormone Receptor Status (%)
ER+ and/or PgR+ | 98 | 98
Both Unknown | 2 | 2
Nodal Status (%)
Node Negative | 50 | 50
Node Positive | 46 | 46
Nodal Status Unknown | 4 | 4
Chemotherapy | 46 | 46

Table 9 shows the study results. Disease-free survival was measured as the time from randomization to the earliest event of loco-regional or distant recurrence of the primary disease or development of contralateral breast cancer or death. Disease-free survival by hormone receptor status, nodal status and adjuvant chemotherapy were similar to the overall results. Data were premature for an analysis of survival.

Table 9: Extended Adjuvant Study Results
 | Femara N = 2582 | Placebo N = 2586 | Hazard Ratio (95% CI) | P-Value
Disease Free Survival (DFS)^1 Events | 122 (4.7%) | 193 (7.5%) | 0.62 (0.49, 0.78)^2 | 0.00003
Local Breast Recurrence | 9 | 22
Local Chest Wall Recurrence | 2 | 8
Regional Recurrence | 7 | 4
Distant Recurrence | 55 | 92 | 0.61 (0.44 - 0.84) | 0.003
Contralateral Breast Cancer | 19 | 29
Deaths Without Recurrence or Contralateral Breast Cancer | 30 | 38
CI = confidence interval for hazard ratio. Hazard ratio of less than 1.0 indicates difference in favor of Femara (lesser risk of recurrence); hazard ratio greater than 1.0 indicates difference in favor of placebo (higher risk of recurrence with Femara).
^1First event of loco-regional recurrence, distant relapse, contralateral breast cancer or death from any cause.
^2Analysis stratified by receptor status, nodal status and prior adjuvant chemotherapy (stratification factors as at randomization). P-value based on stratified log-rank test.

14.3 Updated Analyses of Extended Adjuvant Treatment of Early Breast Cancer, Median Treatment Duration of 60 Months

Table 10: Update of Extended Adjuvant Study Results
 | Femara N = 2582 (%) | Placebo N = 2586 (%) | Hazard Ratio^1 (95% CI) | P-Value^2
Disease Free Survival (DFS) events^3 | 344 (13.3) | 402 (15.5) | 0.89 (0.77, 1.03) | 0.12
Breast cancer recurrence (Protocol definition of DFS events^4) | 209 | 286 | 0.75 (0.63, 0.89) | 0.001
Local Breast Recurrence | 15 | 44
Local Chest Wall Recurrence | 6 | 14
Regional Recurrence | 10 | 8
Distant Recurrence | 140 | 167
Distant Recurrence (first or subsequent events) Contralateral Breast Cancer | 142 37 | 169 53 | 0.88 (0.70,1.10) | 0.246
Deaths Without Recurrence or Contralateral Breast Cancer | 135 | 116
^1Adjusted by receptor status, nodal status and prior chemotherapy.
^2Stratified log-rank test, stratified by receptor status, nodal status and prior chemotherapy.
^3DFS events defined as earliest of loco-regional recurrence, distant metastasis, contralateral breast cancer or death from any cause, and ignoring switches to Femara in 60% of the placebo arm.
^4Protocol definition does not include deaths from any cause.

Updated analyses were conducted at a median follow-up of 62 months. In the Femara arm, 71% of the patients were treated for a least 3 years and 58% of patients completed at least 4.5 years of extended adjuvant treatment. After the unblinding of the study at a median follow-up of 28 months, approximately 60% of the selected patients in the placebo arm opted to switch to Femara.

In this updated analysis shown in Table 10 Femara significantly reduced the risk of breast cancer recurrence or contralateral breast cancer compared with placebo (HR 0.75; 95% CI 0.63, 0.89; P = 0.001). However, in the updated DFS analysis (interval between randomization and earliest event of loco-regional recurrence, distant metastasis, contralateral breast cancer, or death from any cause) the treatment difference was heavily diluted by 60% of the patients in the placebo arm switching to Femara and accounting for 64% of the total placebo patient-years of follow-up. Ignoring these switches, the risk of DFS event was reduced by a non-significant 11% (HR 0.89; 95% CI 0.77, 1.03). There was no significant difference in distant DFS or overall survival.

14.4 First-Line Treatment of Advanced Breast Cancer

A randomized, double-blind, multinational trial (P025) compared Femara 2.5 mg with tamoxifen 20 mg in 916 postmenopausal patients with locally advanced (Stage IIIB or loco-regional recurrence not amenable to treatment with surgery or radiation) or metastatic breast cancer. Time to progression (TTP) was the primary endpoint of the trial. Selected baseline characteristics for this study are shown in Table 11.

Table 11: Selected Study Population Demographics
Baseline Status | Femara | Tamoxifen
 | N = 458 | N = 458
Stage of Disease
IIIB | 6% | 7%
IV | 93% | 92%
Receptor Status
ER and PgR Positive | 38% | 41%
ER or PgR Positive | 26% | 26%
Both Unknown | 34% | 33%
ER^- or PgR^-/Other Unknown | < 1% | 0
Previous Antiestrogen Therapy
Adjuvant | 19% | 18%
None | 81% | 82%
Dominant Site of Disease
Soft Tissue | 25% | 25%
Bone | 32% | 29%
Viscera | 43% | 46%

Femara was superior to tamoxifen in TTP and rate of objective tumor response (see Table 12).

Table 12 summarizes the results of the trial, with a total median follow-up of approximately 32 months. (All analyses are unadjusted and use 2-sided P-values.)

Table 12: Results of First-Line Treatment of Advanced Breast Cancer
 | Femara | Tamoxifen | Hazard or Odds
 | 2.5 mg | 20 mg | Ratio (95% CI)
 | N = 453 | N = 454 | P-Value (2-sided)
Median Time to Progression | 9.4 months | 6.0 months | 0.72 (0.62, 0.83)^1
 |  |  | P < 0.0001
Objective Response Rate
(CR + PR) | 145 (32%) | 95 (21%) | 1.77 (1.31, 2.39)^2
 |  |  | P = 0.0002
(CR) | 42 (9%) | 15 (3%) | 2.99 (1.63, 5.47)^2
 |  |  | P = 0.0004
Duration of Objective Response
Median | 18 months | 16 months
 | (N = 145) | (N = 95)
Overall Survival | 35 months | 32 months
 | (N = 458) | (N = 458) | P = 0.5136^3
^1Hazard ratio.
^2Odds ratio.
^3Overall log-rank test.

Figure 2 shows the Kaplan-Meier curves for TTP.

Figure 2: Kaplan-Meier Estimates of Time to Progression (Study P025)

Table 13 shows results in the subgroup of women who had received prior antiestrogen adjuvant therapy, Table 14, results by disease site and Table 15, the results by receptor status.

Table 13: Efficacy in Patients Who Received Prior Antiestrogen Therapy
Variable | Femara | Tamoxifen
 | 2.5 mg | 20 mg
 | N = 84 | N = 83
Median Time to Progression (95% CI) | 8.9 months (6.2, 12.5) | 5.9 months (3.2, 6.2)
Hazard Ratio for TTP (95% CI) | 0.60 (0.43, 0.84)
Objective Response Rate
(CR + PR) | 22 (26%) | 7 (8%)
Odds Ratio for Response (95% CI) | 3.85 (1.50, 9.60)

Hazard ratio less than 1 or odds ratio greater than 1 favors Femara; hazard ratio greater than 1 or odds ratio less than 1 favors tamoxifen.

Table 14: Efficacy by Disease Site
 | Femara | Tamoxifen
 | 2.5 mg | 20 mg
Dominant Disease Site
Soft Tissue: | N = 113 | N = 115
Median TTP | 12.1 months | 6.4 months
Objective Response Rate | 50% | 34%
Bone: | N = 145 | N = 131
Median TTP | 9.5 months | 6.3 months
Objective Response Rate | 23% | 15%
Viscera: | N = 195 | N = 208
Median TTP | 8.3 months | 4.6 months
Objective Response Rate | 28% | 17%

Table 15: Efficacy by Receptor Status
Variable | Femara | Tamoxifen
 | 2.5 mg | 20 mg
Receptor Positive | N = 294 | N = 305
Median Time to Progression (95% CI) | 9.4 months (8.9, 11.8) | 6.0 months (5.1, 8.5)
Hazard Ratio for TTP (95% CI) | 0.69 (0.58, 0.83)
Objective Response Rate (CR+PR) | 97 (33%) | 66 (22%)
Odds Ratio for Response 95% CI) | 1.78 (1.20, 2.60)
Receptor Unknown | N = 159 | N = 149
Median Time to Progression (95% CI) | 9.2 months (6.1, 12.3) | 6.0 months (4.1, 6.4)
Hazard Ratio for TTP (95% CI) | 0.77 (0.60, 0.99)
Objective Response Rate (CR+PR) | 48 (30%) | 29 (20%)
Odds Ratio for Response (95% CI) | 1.79 (1.10, 3.00)

Hazard ratio less than 1 or odds ratio greater than 1 favors Femara; hazard ratio greater than 1 or odds ratio less than 1 favors tamoxifen.

Figure 3 shows the Kaplan-Meier curves for survival.

Figure 3: Survival by Randomized Treatment Arm

Legend: Randomized Femara: n = 458, events 57%, median overall survival 35 months (95% CI 32 to 38 months)

Randomized tamoxifen: n = 458, events 57%, median overall survival 32 months (95% CI 28 to 37 months)

Overall log-rank P = 0.5136 (i.e., there was no significant difference between treatment arms in overall survival).

The median overall survival was 35 months for the Femara group and 32 months for the tamoxifen group, with a P-value 0.5136. Study design allowed patients to cross over upon progression to the other therapy. Approximately 50% of patients crossed over to the opposite treatment arm and almost all patients who crossed over had done so by 36 months. The median time to crossover was 17 months (Femara to tamoxifen) and 13 months (tamoxifen to Femara). In patients who did not cross over to the opposite treatment arm, median survival was 35 months with Femara (n = 219, 95% CI, 29 to 43 months) vs 20 months with tamoxifen (n = 229, 95% CI, 16 to 26 months).

14.5 Second-Line Treatment of Advanced Breast Cancer

Femara was initially studied at doses of 0.1 mg to 5.0 mg daily in six noncomparative trials (AR/BC1, P01, AR/ST1, AR/PS1, AR/ES1, and NJO-03) in 181 postmenopausal estrogen/progesterone receptor positive or unknown advanced breast cancer patients previously treated with at least antiestrogen therapy. Patients had received other hormonal therapies and also may have received cytotoxic therapy. Eight (20%) of forty patients treated with Femara 2.5 mg daily in trials achieved an objective tumor response (complete or partial response).

Two large randomized, controlled, multinational (predominantly European) trials (AR/BC2, AR/BC3) were conducted in patients with advanced breast cancer who had progressed despite antiestrogen therapy. Patients were randomized to Femara 0.5 mg daily, Femara 2.5 mg daily, or a comparator [megestrol acetate 160 mg daily in one study (AR/BC2); and aminoglutethimide 250 mg twice a day with corticosteroid supplementation in the other study (AR/BC3)]. In each study over 60% of the patients had received therapeutic antiestrogens, and about one-fifth of these patients had an objective response. The megestrol acetate controlled study was double-blind; the other study was open label. Selected baseline characteristics for each study are shown in Table 16.

Table 16: Selected Study Population Demographics
Parameter | Megestrol Acetate | Aminoglutethimide
 | Study | Study
No. of Participants | 552 | 557
Receptor Status
ER/PR Positive | 57% | 56%
ER/PR Unknown | 43% | 44%
Previous Therapy
Adjuvant Only | 33% | 38%
Therapeutic +/- Adj. | 66% | 62%
Sites of Disease
Soft Tissue | 56% | 50%
Bone | 50% | 55%
Viscera | 40% | 44%

Confirmed objective tumor response (complete response plus partial response) was the primary endpoint of the trials. Responses were measured according to the Union Internationale Contre le Cancer (UICC) criteria and verified by independent, blinded review. All responses were confirmed by a second evaluation 4 to 12 weeks after the documentation of the initial response.

Table 17 shows the results for the first trial (AR/BC2), with a minimum follow-up of 15 months that compared Femara 0.5 mg, Femara 2.5 mg, and megestrol acetate 160 mg daily (All analyses are unadjusted).

Table 17: Megestrol Acetate Study Results
 | Femara | Femara | Megestrol
 | 0.5 mg | 2.5 mg | Acetate
 | N = 188 | N = 174 | N = 190
Objective Response (CR + PR) | 22 (11.7%) | 41 (23.6%) | 31 (16.3%)
Median Duration of Response | 552 days | (Not reached) | 561 days
Median Time to Progression | 154 days | 170 days | 168 days
Median Survival | 633 days | 730 days | 659 days
Odds Ratio for Response | Femara 2.5: Femara 0.5 = 2.33 |  | Femara 2.5: megestrol = 1.58
 | (95% CI: 1.32, 4.17); P = 0.004* |  | (95% CI: 0.94, 2.66); P = 0.08*
Relative Risk of Progression | Femara 2.5: Femara 0.5 = 0.81 |  | Femara 2.5: megestrol = 0.77
 | (95% CI: 0.63, 1.03); P = 0.09* |  | (95% CI: 0.60, 0.98); P = 0.03*
*Two-sided P-value.

The Kaplan-Meier curves for progression for the megestrol acetate study are shown in Figure 4.

Figure 4: Kaplan-Meier Estimates of Time to Progression (Megestrol Acetate Study)

The results for the study comparing Femara to aminoglutethimide (AR/BC3), with a minimum follow-up of 9 months, are shown in Table 18 (Unadjusted analyses are used).

Table 18: Aminoglutethimide Study Results
 | Femara | Femara
 | 0.5 mg | 2.5 mg | Aminoglutethimide
 | N = 193 | N = 185 | N = 179
Objective Response (CR + PR) | 34 (17.6%) | 34 (18.4%) | 22 (12.3%)
Median Duration of Response | 619 days | 706 days | 450 days
Median Time to Progression | 103 days | 123 days | 112 days
Median Survival | 636 days | 792 days | 592 days
Odds Ratio for Response | Femara 2.5: |  | Femara 2.5:
 | Femara 0.5 = 1.05 |  | Aminoglutethimide = 1.61
 | (95% CI: 0.62, 1.79); P = 0.85* |  | (95% CI: 0.90, 2.87); P = 0.11*
Relative Risk of Progression | Femara 2.5: |  | Femara 2.5:
 | Femara 0.5 = 0.86 |  | Aminoglutethimide = 0.74
 | (95% CI: 0.68, 1.11); P = 0.25* |  | (95% CI: 0.57, 0.94); P = 0.02*
*Two-sided P-value.

The Kaplan-Meier curves for progression for the aminoglutethimide study is shown in Figure 5.

Figure 5: Kaplan-Meier Estimates of Time to Progression (Aminoglutethimide Study)

16 HOW SUPPLIED/STORAGE AND HANDLING

Packaged in HDPE bottles with a safety screw cap.

2.5 mg tablets

Bottles of 30 tablets NDC 0078-0249-15

Store at 20°C to 25°C (68°F to 77°F); excursions are permitted between 15°C and 30°C (59°F and 86°F) [see USP Controlled Room Temperature].

17 PATIENT COUNSELING INFORMATION

Embryo-Fetal Toxicity

Advise females of reproductive potential of the potential risk to a fetus and to use effective contraception during Femara therapy and for at least 3 weeks after the last dose. Advise females to contact their healthcare provider if they become pregnant, or if pregnancy is suspected, during treatment with Femara [see Warnings and Precautions (5.6) and Use in Specific Populations (8.1, 8.3)].

Lactation

Advise women not to breastfeed during Femara treatment and for at least 3 weeks after the last dose [see Use in Specific Populations (8.2)].

Infertility

Advise females and males of reproductive potential of the potential for reduced fertility from Femara [see Use in Specific Populations (8.3)].

Fatigue and Dizziness

Since fatigue and dizziness have been observed with the use of Femara and somnolence was uncommonly reported, caution is advised when driving or using machinery [see Warnings and Precautions (5.4)].

Bone Effects

Consideration should be given to monitoring bone mineral density [see Warnings and Precautions (5.1)].

Distributed by:
Novartis Pharmaceuticals Corporation
East Hanover, New Jersey, 07936

© Novartis

T2024-86

PRINCIPAL DISPLAY PANEL

NDC 0078-0249-15

Femara®
(letrozole tablets)

2.5 mg per tablet

Rx only

30 Tablets

NOVARTIS